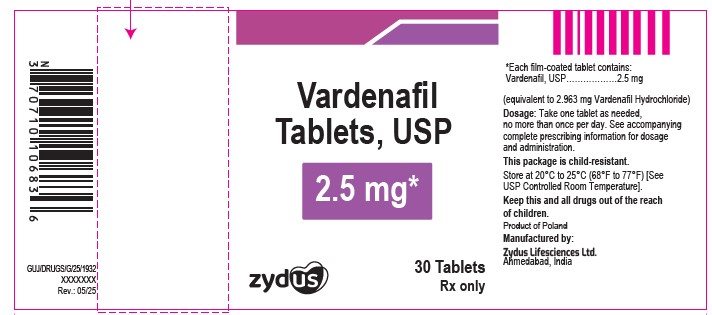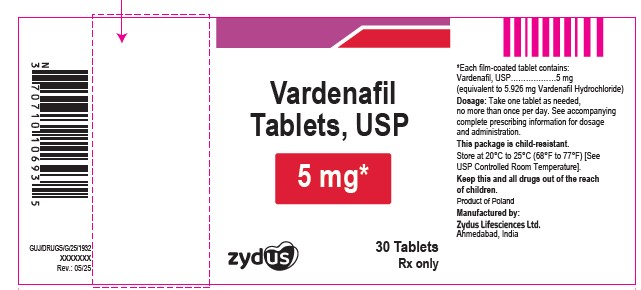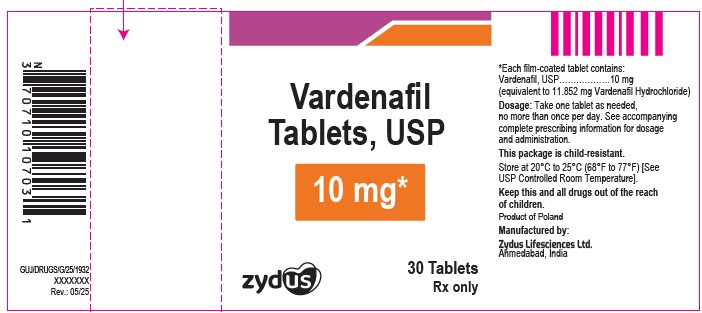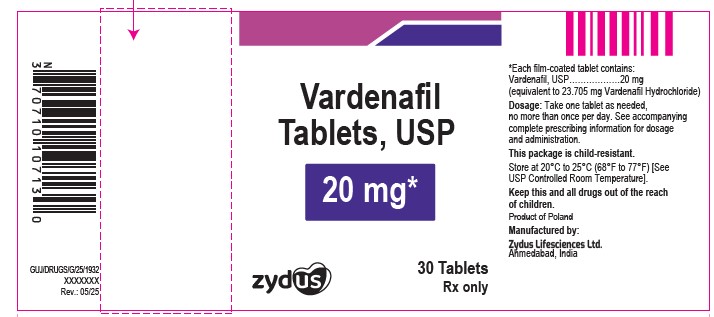 DRUG LABEL: VARDENAFIL
NDC: 70771-1047 | Form: TABLET, FILM COATED
Manufacturer: Zydus Lifesciences Limited
Category: prescription | Type: HUMAN PRESCRIPTION DRUG LABEL
Date: 20260105

ACTIVE INGREDIENTS: VARDENAFIL HYDROCHLORIDE TRIHYDRATE 2.5 mg/1 1
INACTIVE INGREDIENTS: CELLULOSE, MICROCRYSTALLINE; HYPROMELLOSES; POLYETHYLENE GLYCOL, UNSPECIFIED; SILICON DIOXIDE; SODIUM STEARYL FUMARATE; STARCH, CORN; TITANIUM DIOXIDE

VARDENAFIL TABLETS USP, for oral use

PACKAGE LABEL.PRINCIPAL DISPLAY PANEL

NDC 70771-1047-3

Vardenafil Tablets USP, 2.5 mg

30 Tablets

Rx only

NDC 70771-1048-3

Vardenafil Tablets USP, 5 mg

30 Tablets

Rx only

NDC 70771-1049-3

Vardenafil Tablets USP, 10 mg

30 Tablets

Rx only

NDC 70771-1050-3

Vardenafil Tablets USP, 20 mg

30 Tablets

Rx only